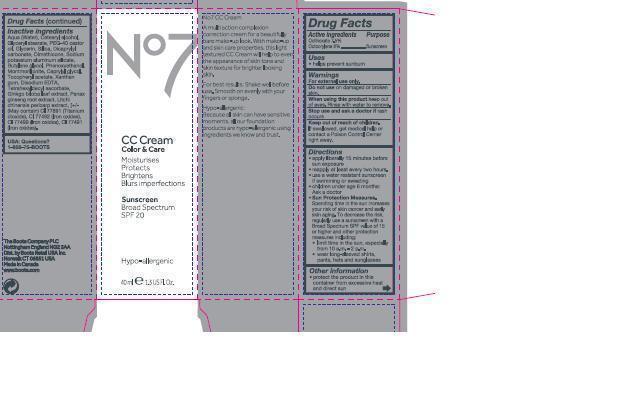 DRUG LABEL: No7 CC Cream Medium
NDC: 68472-160 | Form: EMULSION
Manufacturer: Boots Retail USA Inc
Category: otc | Type: HUMAN OTC DRUG LABEL
Date: 20140401

ACTIVE INGREDIENTS: OCTOCRYLENE 3.2 g/40 g; OCTINOXATE 3 g/40 g
INACTIVE INGREDIENTS: WATER; GLYCERYL STEARATE SE; PEG-40 CASTOR OIL; GLYCERIN; DICAPRYLYL CARBONATE; DIMETHICONE; BUTYLENE GLYCOL; MONTMORILLONITE; XANTHAN GUM; TETRAHEXYLDECYL ASCORBATE; GINKGO BILOBA LEAF OIL; PANAX GINSENG ROOT OIL; CAPRYLYL GLYCOL; PHENOXYETHANOL; TITANIUM DIOXIDE

No7 CC Cream Medium

Carton Active Ingredients Section

Active ingredients

Octinoxate 7.5%

Octocrylene 8%

Purpose Sunscreen

Uses

Uses - helps prevent sunburn

WARNINGS AND PRECAUTIONS

For external use only

Do not use on damaged or broken skin

When using this product keep out of eyes. Rinse with water to remove.

Ask a doctor

Stop use and ask a doctor if rash occurs

Keep out of reach of children. If swallowed, get medical help or contact a Poison Control Center right away

Directions

apply liberally 15 minutes before sun exposure

reapply at least every two hours

use a water resistant sunscreen if swimming or sweating

children under 6 months of age: Ask a doctor

Sun Protection Measures. spending time in the sun increases your risk of skin cancer and early skin aging. To decrease the risk, regularly use a sunscreen with a Broad Spectrum SPF value of 15 or higher and other protection measures including:

limit time in the sun, especially from 10 a.m. - 2 p.m.

wear long-sleeved shirts, pants, hats and sunglasses.

Storage

Other information - protect the product in this container from excessive heat and direct sun

Inactive ingredients

Aqua(Water), Cetearyl alcohol, Glyceryl stearate, PEG-40 castor oil, Glycerin, Silica, Dicaprylyl carbonate, Dimethicone, Sodium potassium aluminum silicate, Butylene glycol, Phenoxyethanol, Montmorillonite, Caprylyl glycol, Tocopheryl acetate, Xanthan gum, Disodium EDTA, Tetrahexyldecyl ascorbate, Ginkgo biloba leaf extract, Litchi chinensis pericarp extract CI 77891 (Titanium dioxide), CI 77492 (Iron oxides) CI 77491 (Iron oxides), CI 77499 (Iron oxides)

Description

No7 CC Cream

A multi action complexion correction cream for a beautifully bare make up look. With make-up and skincare properties, this light textured CC Cream will help to even the appearance of skin tone and skin texture for brighter looking skin. For best results: Shake well before use. Smooth on evenly with your fingers or sponge.

Information

The Boots Company PLC

Nottingham England NG2 3AA

Dist by Boots Retail USA Inc.

Norwalk CT 06851 USA

Made in Canada

www.boots.com

Tube

No7 CC Cream

Sunscreen

Broad Spectrum SPF 20

40ml e 1.3 US Fl.Oz.

Warnings

Avoid contact with eyes. If product gets into the eyes, rinse well with water immediately

Description

A multi action complexion correction cream for a beautifully bare make-up look. With make-up and skin care properties, this CC Cream will help to even the appearance of skin tone and skin texture for brighter looking skin.

Information

The Boots Company PLC

The Boots Company PLC

Nottingham England NG2 3AA

Dist by Boots Retail USA Inc.

Norwalk CT 06851 USA

Made in Canada

www.boots.com